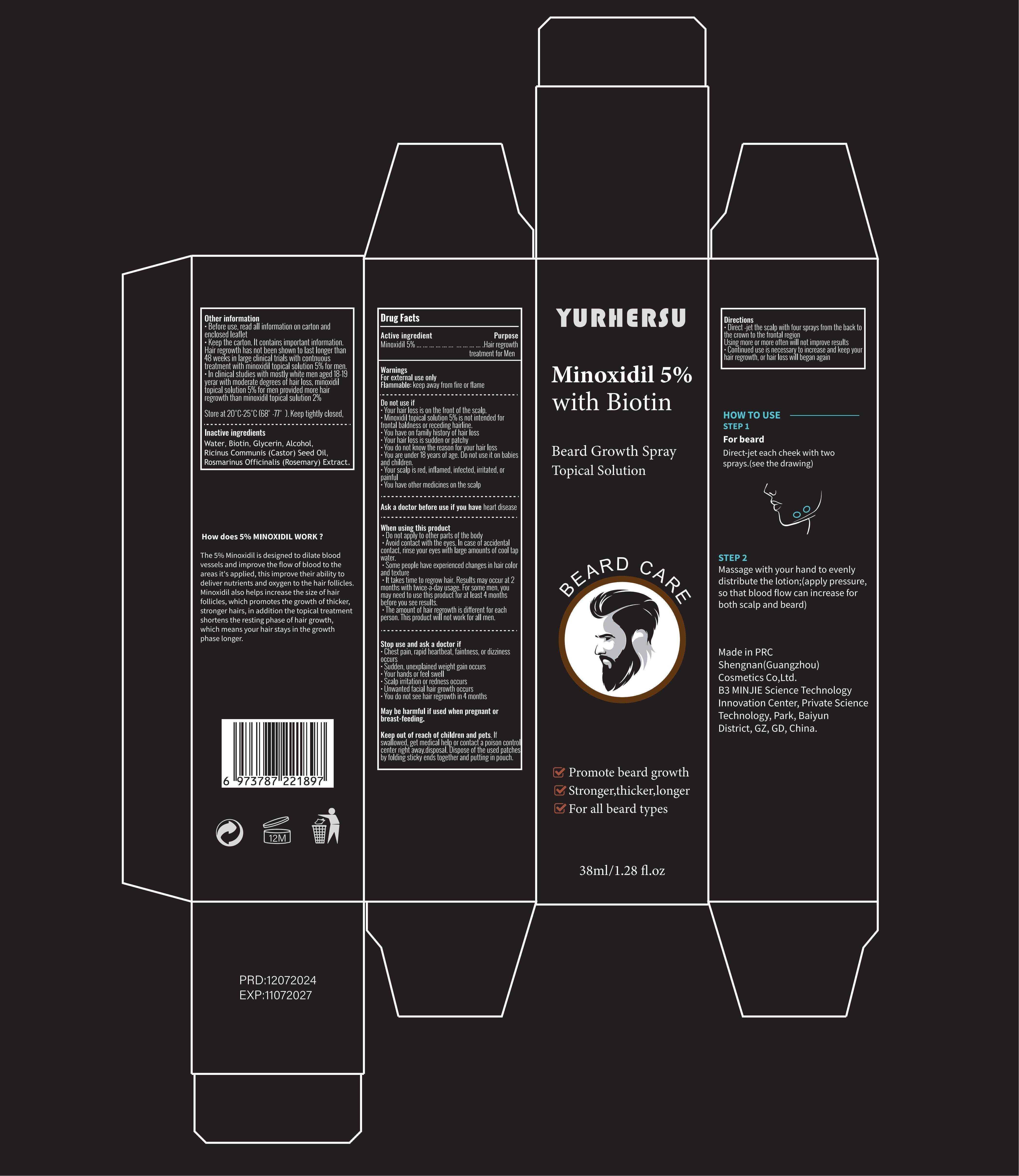 DRUG LABEL: Beard Care
NDC: 84019-006 | Form: LOTION
Manufacturer: Shengnan (Guangzhou) Cosmetics Co., LTD
Category: otc | Type: HUMAN OTC DRUG LABEL
Date: 20240706

ACTIVE INGREDIENTS: MINOXIDIL 5 g/100 mL
INACTIVE INGREDIENTS: WATER; GLYCERIN; BIOTIN; CASTOR OIL; ROSEMARY OIL; ALCOHOL

Beard Care

ACTIVE INGREDIENT

Minoxidil 5%

PURPOSE

FOR STRONGER THICKER FULLER HAIR

INDICATIONS

RESTORE THINNING & WEAK HAIR

WARNINGS

For external use only

DO NOT USE SECTION

Pregnant women and children are advised not to use, and do not use if there are wounds.

WHEN USING SECTION

Spray: evenly spray the spray on the beard area that needs hair growth. Generally speaking, maintain a distance of about 10 to 15 centimeters (4 to 6 inches) when using to avoid waste and excessive spraying.

Massage: Use fingertips to gently massage the spray liquid evenly on the beard to ensure that the product penetrates into the hair follicle.

STOP USE

If you experience any discomfort after use, please stop using and seek medical help promptly.

KEEP OUT OF REACH OF CHILDREN SECTION

DOSAGE

Apply directly to the area that needsimprovement
Using more often will not improve results.
Continued use is necessary toincrease and keep your hair regrowth,or hair loss will began again.

STORAGE

Store in a dark and cool place.

INGREDIENT

Water
PROPANEDIOL
Glycerin
Alcohol
Castor Oil
Biotin
Rosemary Oil